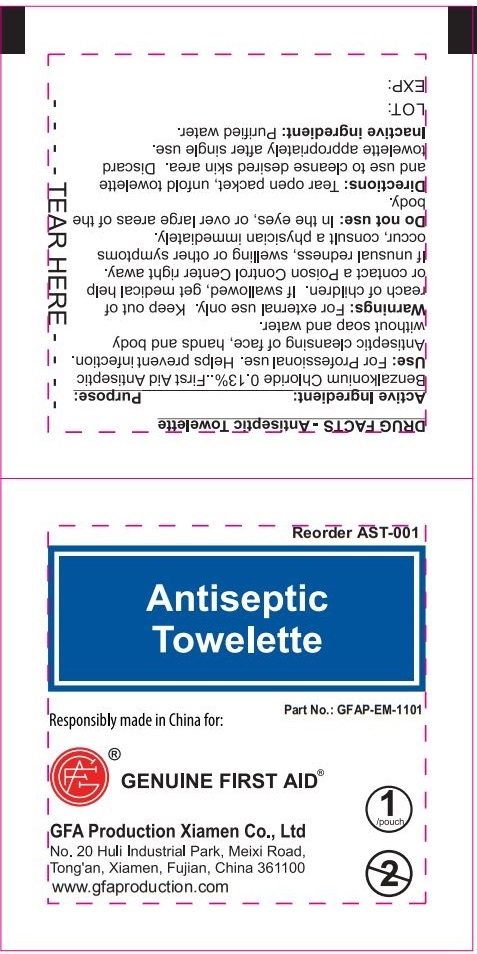 DRUG LABEL: Genuine First Aid Antiseptic Towelette
NDC: 50814-057 | Form: SWAB
Manufacturer: GFA Production (Xiamen) Co., Ltd.
Category: otc | Type: HUMAN OTC DRUG LABEL
Date: 20241015

ACTIVE INGREDIENTS: BENZALKONIUM CHLORIDE 1.3 mg/1 mL
INACTIVE INGREDIENTS: WATER

Genuine First Aid Antiseptic Towelette

Active Ingredient:

Benzalkonium Chloride 0.13%

Purpose:

First Aid Antiseptic

Use:

For Professional use. Helps prevent infection. Antiseptic cleansing of face, hands and body with out soap and water.

Warnings:

For external use only.

Keep out of reach of children.

If swallowed, get medical help or contact a Poison Control Center right away. If unusual redness, swelling or other symptoms occur, consult a physician immediately.

Do not use:

In the eyes, or over large areas of the body.

Directions:

Tear open packet, unfold towelette and use to cleanse desired skin area. Discard towelette appropriately after single use.

Inactive ingredient:

Purified water.